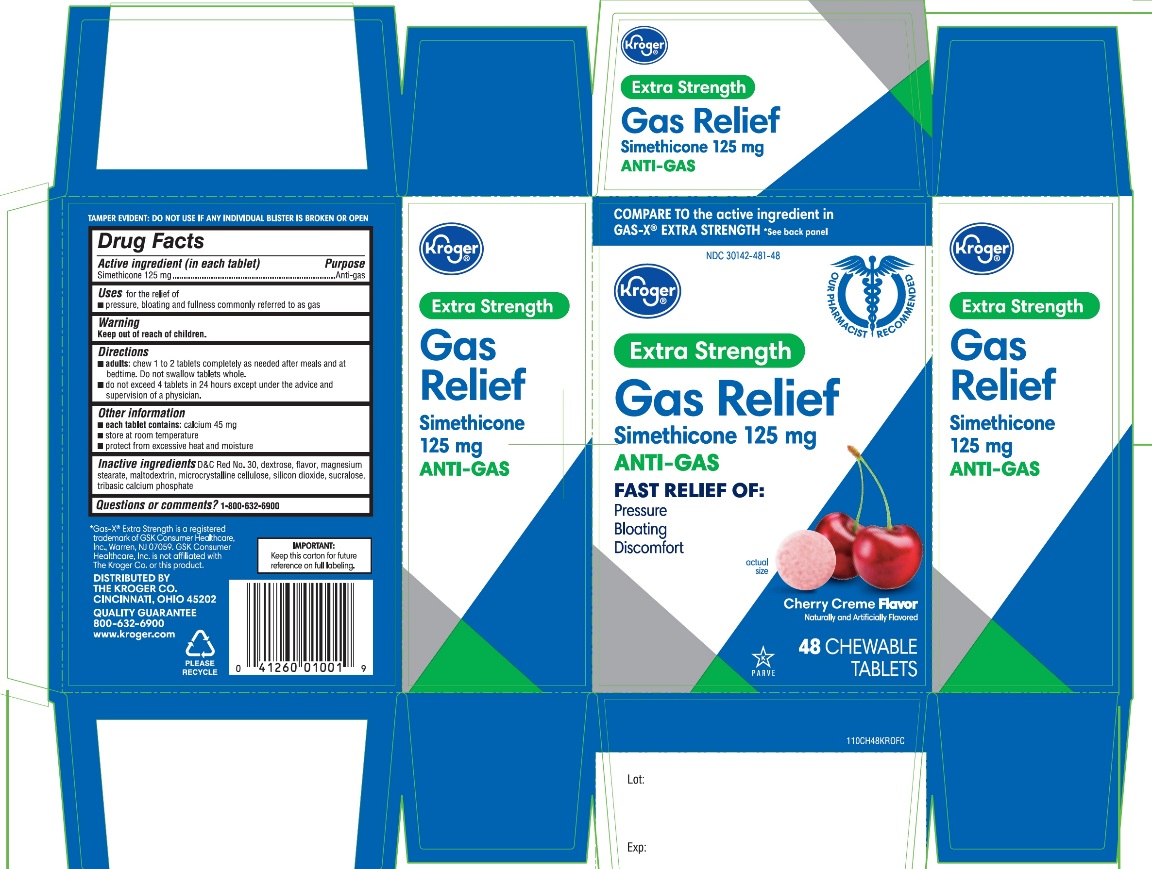 DRUG LABEL: Kroger Extra Strength

NDC: 30142-481 | Form: TABLET, CHEWABLE
Manufacturer: KROGER COMPANY
Category: otc | Type: HUMAN OTC DRUG LABEL
Date: 20250801

ACTIVE INGREDIENTS: DIMETHICONE, UNSPECIFIED 125 mg/1 1
INACTIVE INGREDIENTS: SUCRALOSE; TRIBASIC CALCIUM PHOSPHATE; D&C RED NO. 30; DEXTROSE, UNSPECIFIED FORM; MAGNESIUM STEARATE; MALTODEXTRIN; MICROCRYSTALLINE CELLULOSE; SILICON DIOXIDE

Kroger Extra Strength Gas Relief Simethicone

Active ingredient (in each tablet)

Simethicone 125 mg

Purpose

Anti-gas

Uses

for the relief of

- pressure, bloating and fullness commonly referred to as gas

Directions

- adults: chew 1 to 2 tablets as needed after meals and at bedtime. Do not swallow tablets whole.
- do not exceed 4 tablets in a 24 hours except under the advice and supervision of a physician.

Other information

- each tablets contains:calcium 45 mg
- store at room temperature
- protect from excessive heat and moisture

TAMPER EVIDENT: DO NOT USE IF ANY INDVIDUAL BLISTER IS BROKEN OR OPEN

Inactive ingredients

D&C Red No. 30, dextrose, flavor, magnesium stearate, maltodextrin, microcrystalline cellulose, silicon dioxide, sucralose, tribasic calcium phosphate.

Principal Display Panel

NDC 30142-481-48

*Compare to the active ingredient in GAS-X®Extra Strength

Extra Strength

Gas Relief

Simethicone//Anti-gas

For Fast Relief of Pressure,

Bloating & Gas Distress

Cherry Creme Flavor

Naturally and Artificially Flavored

48 Chewable Tablets

Distributed by:

*This product is not manufactured or distributed by GSK Consumer Healthcare, Inc., the distributor of Gas-X®Extra strength.

IMPORTANT:Keep this carton for future reference on full labeling.